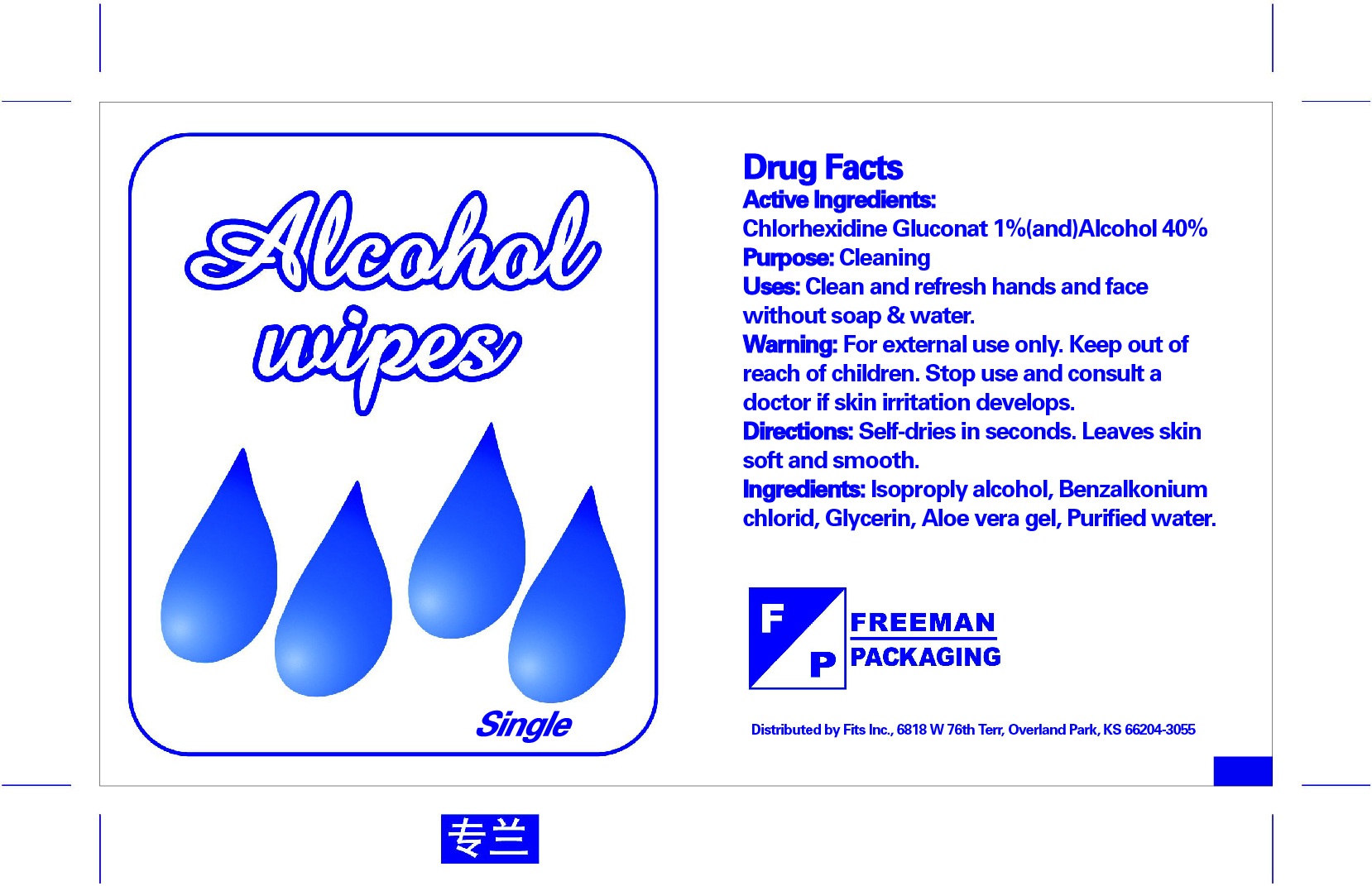 DRUG LABEL: Freeman Packing Alcohol Wipe
NDC: 67772-018 | Form: LIQUID
Manufacturer: Jiangxi Sencen Hygienic Products Co., Ltd.
Category: otc | Type: HUMAN OTC DRUG LABEL
Date: 20160717

ACTIVE INGREDIENTS: ALCOHOL 40 g/100 g; CHLORHEXIDINE GLUCONATE 1 g/100 g
INACTIVE INGREDIENTS: WATER; ISOPROPYL ALCOHOL; ALOE VERA WHOLE; GLYCERIN; BENZALKONIUM CHLORIDE

Drug Fact

Active Ingredient

Chlorhexidine Gluconate........................1%

Alcohol....................................................40%

Purpose:

Cleaning

Uses:

Clean and refresh hands and face without soap and water

Warnings:

For external use on hands only. Store in a cool place. Stop use and ask for doctor if skin irritation developes

Keep out of reach of children

Directions:

Self dries in second. Leaves skin soft and smooth

STORAGE AND HANDLING

Store in a cool place

Inactive Ingredient:

Isopropyl Alcohol, Benzalkonium Chloride, Glycerin, Aloe Vera Gel, Purified Water